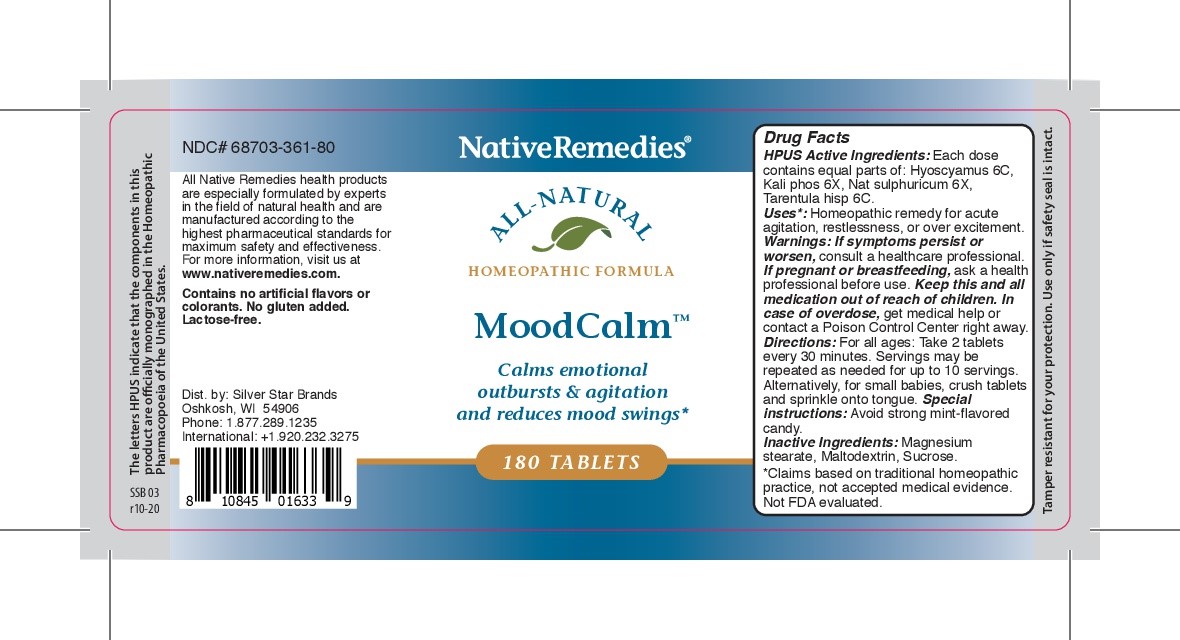 DRUG LABEL: MoodCalm
NDC: 68703-361 | Form: TABLET
Manufacturer: Silver Star Brands
Category: homeopathic | Type: HUMAN OTC DRUG LABEL
Date: 20250101

ACTIVE INGREDIENTS: LYCOSA TARANTULA 6 [hp_C]/180 1; SODIUM SULFATE 6 [hp_X]/180 1; HYOSCYAMUS NIGER LEAF 6 [hp_C]/180 1; POTASSIUM PHOSPHATE, DIBASIC 6 [hp_X]/180 1
INACTIVE INGREDIENTS: MALTODEXTRIN; SUCROSE; MAGNESIUM STEARATE

NativeRemedies® MoodCalm™

HPUS Active Ingredients: Hyoscyamus 6C, Kali phos 6X, Nat sulphuricum 6X, Tarentula hisp 6C.

Uses*

Uses*: Homeopathic remedy for acute agittion, restlessness, or over excitement.

Warnings

Warnings: If symptoms persist or worsen, consult a healthcare professional. If pregnant or breastfeeding, ask a health professional before use. Keep this and all medicatoin out of reach of children. In case of overdose, ge medical help or contact a Poison Control Center right away.

Directions

Directions: For all ages: Take 2 tablets every 30 minutes. Servings may be repeated as needed for up to 10 servings. Alternatively, for small babies, crush tablets and sprinkle onto tongue.

Special instructions: Avoid strong mint-flavored candy.

OTHER SAFETY INFORMATION

Tamper resistant for your protection. Use only if safety seal is intact.

Contains no artificai flavors or colorants. No gluten added. Lactose-free.

Inactive Ingredients

Inactive Ingredients: Magnesium stearate, Maltodextrin, Sucrose.

KEEP OUT OF REACH OF CHILDREN

Keep this and all medication out of reach of children.

PREGNANCY OR BREAST FEEDING

If pregnant or breastfeeding, ask a health professional before use. Keep this and all medication out of reach of children. In case of overdose, get medical help or contact a Poison Control Center right away.

PURPOSE

Calms emotional outbursts & agitation and reduces mood swings. *

*Claims based on traditional homeopathic practice, not accepted medical evidence. Not FDA evaluated.